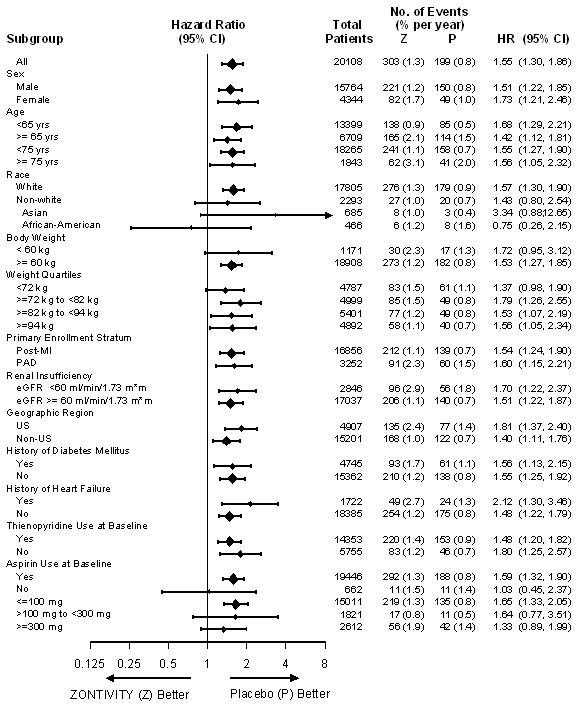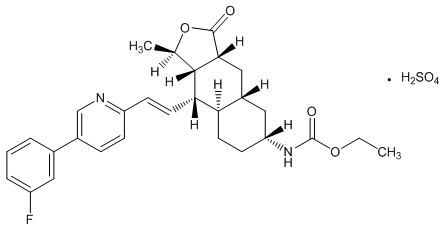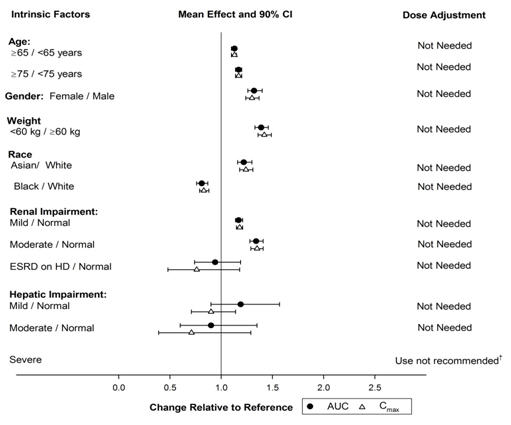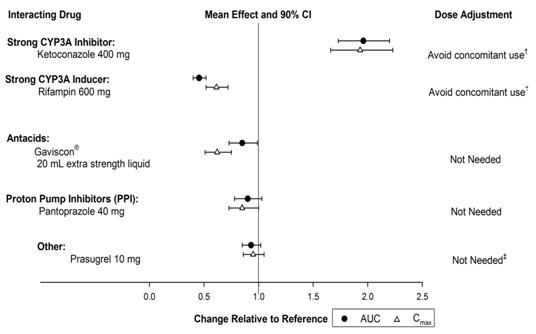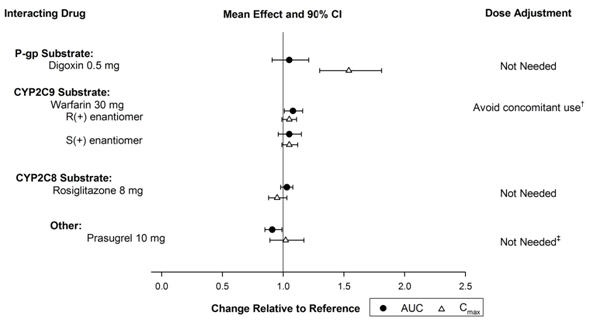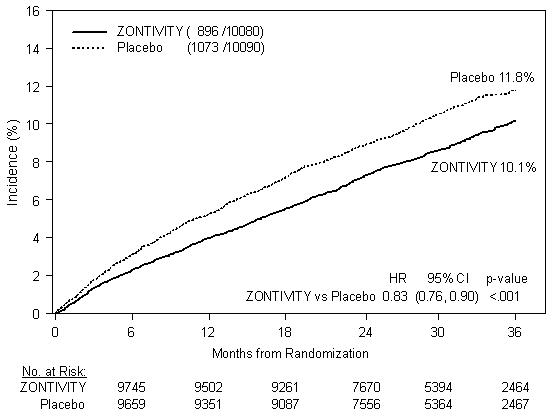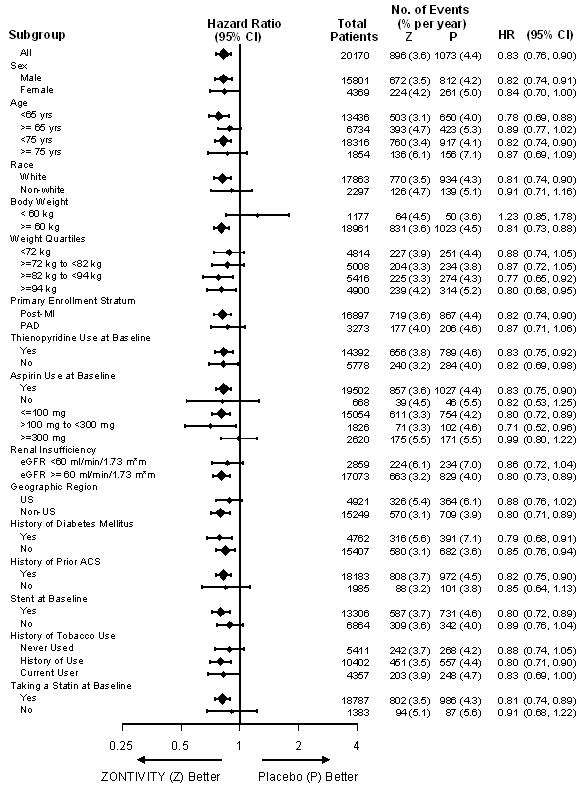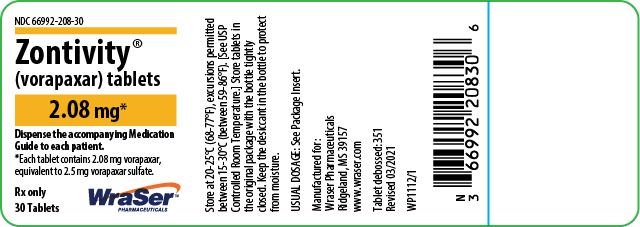 DRUG LABEL: ZONTIVITY
NDC: 66992-208 | Form: TABLET, FILM COATED
Manufacturer: WraSer Pharmaceuticals, LLC
Category: prescription | Type: HUMAN PRESCRIPTION DRUG LABEL
Date: 20221018

ACTIVE INGREDIENTS: VORAPAXAR SULFATE 2.08 mg/1 1
INACTIVE INGREDIENTS: LACTOSE MONOHYDRATE; CELLULOSE, MICROCRYSTALLINE; CROSCARMELLOSE SODIUM; POVIDONE; MAGNESIUM STEARATE; HYPROMELLOSE 2910 (15 MPA.S); TITANIUM DIOXIDE; TRIACETIN; FERRIC OXIDE YELLOW

HIGHLIGHTS OF PRESCRIBING INFORMATION

These highlights do not include all the information needed to use ZONTIVITY safely and effectively. See full prescribing information for ZONTIVITY.
ZONTIVITY® (vorapaxar) Tablets 2.08 mg*, for oral use
*Equivalent to 2.5 mg vorapaxar sulfate
Initial U.S. Approval: 2014

WARNING: BLEEDING RISK

See full prescribing information for complete boxed warning.

- Do not use ZONTIVITY in patients with a history of stroke, transient ischemic attack (TIA), or intracranial hemorrhage (ICH); or active pathological bleeding. (4.1, 4.2)
- Antiplatelet agents, including ZONTIVITY, increase the risk of bleeding, including ICH and fatal bleeding. (5.1)

1 INDICATIONS AND USAGE

ZONTIVITY is a protease-activated receptor-1 (PAR-1) antagonist indicated for the reduction of thrombotic cardiovascular events in patients with a history of myocardial infarction (MI) or with peripheral arterial disease (PAD). ZONTIVITY has been shown to reduce the rate of a combined endpoint of cardiovascular death, MI, stroke, and urgent coronary revascularization. (1.1)

2 DOSAGE AND ADMINISTRATION

- One tablet of ZONTIVITY orally once daily. (2.1)
- Use with aspirin and/or clopidogrel according to their indications or standard of care. There is limited clinical experience with other antiplatelet drugs and none with ZONTIVITY as the only antiplatelet agent. (2.2)

3 DOSAGE FORMS AND STRENGTHS

Tablets: 2.08 mg vorapaxar. (3)

4 CONTRAINDICATIONS

- History of stroke, TIA, or ICH. (4.1)
- Active pathologic bleeding. (4.2)

5 WARNINGS AND PRECAUTIONS

- Like other antiplatelet agents, ZONTIVITY increases the risk of bleeding. (5.1)
- Avoid use with strong CYP3A inhibitors or inducers. (5.2)

6 ADVERSE REACTIONS

- Bleeding, including life-threatening and fatal bleeding, is the most commonly reported adverse reaction. (6.1)

To report SUSPECTED ADVERSE REACTIONS, contact WraSer Pharmaceuticals at 1-800-988-6115 or FDA at 1-800-FDA-1088 or www.fda.gov/medwatch.

8 USE IN SPECIFIC POPULATIONS

- Pregnancy: When pregnancy is detected, discontinue vorapaxar and initiate appropriate alternative therapy. (8.1)
- Lactation: Breastfeeding not recommended. (8.2)

FULL PRESCRIBING INFORMATION

WARNING: BLEEDING RISK

- Do not use ZONTIVITY in patients with a history of stroke, transient ischemic attack (TIA), or intracranial hemorrhage (ICH); or active pathological bleeding [see CONTRAINDICATIONS (4.1, 4.2)] .
- Antiplatelet agents, including ZONTIVITY, increase the risk of bleeding, including ICH and fatal bleeding [see Warnings and Precautions (5.1)].

1 INDICATIONS AND USAGE

1.1 Patients with History of Myocardial Infarction (MI) or with Peripheral Arterial Disease (PAD)

ZONTIVITY ® is indicated for the reduction of thrombotic cardiovascular events in patients with a history of myocardial infarction (MI) or with peripheral arterial disease (PAD). ZONTIVITY has been shown to reduce the rate of a combined endpoint of cardiovascular death, MI, stroke, and urgent coronary revascularization (UCR).

2 DOSAGE AND ADMINISTRATION

2.1 General Dosing Information

Take one tablet of ZONTIVITY 2.08 mg orally once daily, with or without food.

2.2 Coadministration with Other Antiplatelet Drugs

There is no experience with use of ZONTIVITY alone as the only administered antiplatelet agent. ZONTIVITY has been studied only as an addition to aspirin and/or clopidogrel. Use ZONTIVITY with aspirin and/or clopidogrel according to their indications or standard of care [see Clinical Studies (14)] . There is limited clinical experience with other antiplatelet drugs.

3 DOSAGE FORMS AND STRENGTHS

ZONTIVITY tablets, 2.08 mg vorapaxar, are yellow, oval-shaped, film-coated tablets with "351" on one side.

4 CONTRAINDICATIONS

4.1 History of Stroke, Transient Ischemic Attack (TIA), or Intracranial Hemorrhage (ICH)

ZONTIVITY is contraindicated in patients with a history of stroke, TIA, or ICH because of an increased risk of ICH in this population [see Adverse Reactions (6)] .

Discontinue ZONTIVITY in patients who experience a stroke, TIA, or ICH [see Adverse Reactions (6.1) and Clinical Studies (14)] .

4.2 Active Pathologic Bleeding

ZONTIVITY is contraindicated in patients with active pathological bleeding such as ICH or peptic ulcer [see Warnings and Precautions (5.1) and Adverse Reactions (6.1)] .

5 WARNINGS AND PRECAUTIONS

5.1 General Risk of Bleeding

Antiplatelet agents, including ZONTIVITY, increase the risk of bleeding, including ICH and fatal bleeding [see Adverse Reactions (6.1)] .

ZONTIVITY increases the risk of bleeding in proportion to the patient's underlying bleeding risk. Consider the underlying risk of bleeding before initiating ZONTIVITY. General risk factors for bleeding include older age, low body weight, reduced renal or hepatic function, history of bleeding disorders, and use of certain concomitant medications (e.g., anticoagulants, fibrinolytic therapy, chronic nonsteroidal anti-inflammatory drugs [NSAIDS], selective serotonin reuptake inhibitors, serotonin norepinephrine reuptake inhibitors) increases the risk of bleeding [see Use in Specific Populations (8.7) and Clinical Pharmacology (12.3)] . Avoid concomitant use of warfarin or other anticoagulants.

Suspect bleeding in any patient who is hypotensive and has recently undergone coronary angiography, percutaneous coronary intervention (PCI), coronary artery bypass graft surgery (CABG), or other surgical procedures.

Withholding ZONTIVITY for a brief period will not be useful in managing an acute bleeding event because of its long half-life. There is no known treatment to reverse the antiplatelet effect of ZONTIVITY. Significant inhibition of platelet aggregation remains 4 weeks after discontinuation [see Overdosage (10) and Clinical Pharmacology (12.2, 12.3)].

5.2 Strong CYP3A Inhibitors or Inducers

Strong CYP3A inhibitors increase and inducers decrease ZONTIVITY exposure. Avoid concomitant use of ZONTIVITY with strong CYP3A inhibitors or inducers [see Drug Interactions (7.1) and Clinical Pharmacology (12.3)] .

6 ADVERSE REACTIONS

The following serious adverse reaction is also discussed elsewhere in the labeling:

- Bleeding [see Boxed Warning and Warnings and Precautions (5.1)] .

6.1 Clinical Trials Experience

Because clinical trials are conducted under widely varying conditions, adverse reaction rates observed in the clinical trials of a drug cannot be directly compared to rates in the clinical trials of another drug and may not reflect the rates observed in clinical practice.

ZONTIVITY was evaluated for safety in 13,186 patients, including 2,187 patients treated for more than 3 years, in the Phase 3 study TRA 2°P TIMI 50 (Thrombin Receptor Antagonist in Secondary Prevention of Atherothrombotic Ischemic Events). The overall study population, patients who had evidence or a history of atherosclerosis involving the coronary (post-MI), cerebral (ischemic stroke), or peripheral vascular (documented history of PAD) systems, was treated once a day with ZONTIVITY (n=13,186) or placebo (n=13,166). Patients randomized to ZONTIVITY received treatment for a median of 2.3 years.

The adverse events in the ZONTIVITY-treated (n=10,059) and placebo-treated (n=10,049) post-MI or PAD patients with no history of stroke or TIA are shown below [see Contraindications (4)] .

Bleeding
GUSTO severe bleeding was defined as fatal, intracranial, or bleeding with hemodynamic compromise requiring intervention; GUSTO moderate bleeding was defined as bleeding requiring transfusion of whole blood or packed red blood cells without hemodynamic compromise. (GUSTO: Global Utilization of Streptokinase and Tissue Plasminogen Activator for Occluded Arteries.)

The results for the bleeding endpoints in the post-MI or PAD patients without a history of stroke or TIA are shown in Table 1. ZONTIVITY increased GUSTO moderate or severe bleeding by 55%.

Table 1: Non-CABG-Related Bleeds in Post-MI or PAD Patients without a History of Stroke or TIA (First Dose to Last Dose + 30 Days) in the TRA 2°P Study
 | Placebo (n=10,049) |  | ZONTIVITY (n=10,059)
Endpoints | Patients with events (%) | K-M % [K-M estimate at 1,080 days.] | Patients with events (%) | K-M % | Hazard Ratio [Clinically significant bleeding includes any bleeding requiring medical attention including ICH, or clinically significant overt signs of hemorrhage associated with a drop in hemoglobin (Hgb) of ≥3 g/dL (or, when Hgb is not available, an absolute drop in hematocrit (Hct) of ≥9%).] , [Hazard ratio is ZONTIVITY group vs. placebo group.] (95% CI)
GUSTO Bleeding Categories
Severe | 82 (0.8%) | 1.0% | 100 (1.0%) | 1.3% | 1.24 (0.92 - 1.66)
Moderate or Severe | 199 (2.0%) | 2.4% | 303 (3.0%) | 3.7% | 1.55 (1.30 - 1.86)
Any GUSTO Bleeding (Severe/Moderate/Mild) | 1769 (17.6%) | 19.8% | 2518 (25.0%) | 27.7% | 1.52 (1.43 - 1.61)
Fatal Bleeding | 14 (0.1%) | 0.2% | 16 (0.2%) | 0.2% | 1.15 (0.56 - 2.36)
Intracranial Hemorrhage (ICH) | 31 (0.3%) | 0.4% | 45 (0.4%) | 0.6% | 1.46 (0.92-2.31)
Clinically Significant Bleeding | 950 (9.5%) | 10.9% | 1349 (13.4%) | 15.5% | 1.47 (1.35 - 1.60)
Gastrointestinal Bleeding | 297 (3.0%) | 3.5% | 400 (4.0%) | 4.7% | 1.37 (1.18-1.59)

The effects of ZONTIVITY on bleeding were examined in a number of subsets based on demographic and other baseline characteristics. Many of these are shown in Figure 1. Such analyses must be interpreted cautiously, as differences can reflect the play of chance among a large number of analyses.

Figure 1: Subgroup Analyses (GUSTO Moderate or Severe Bleeding) in Post-MI or PAD Patients without a History of Stroke or TIA in the TRA 2°P Study (First Dose to Last Dose + 30 Days)

In TRA 2°P, 367 post-MI or PAD patients without a history of stroke or TIA underwent CABG surgery. Study investigators were encouraged not to discontinue treatment with study drug (i.e., ZONTIVITY or placebo) prior to surgery. Approximately 12.3% of patients discontinued ZONTIVITY more than 30 days prior to CABG. The relative risk for GUSTO moderate or severe bleeding was approximately 1.2 on ZONTIVITY vs. placebo.

Bleeding events that occurred on ZONTIVITY were treated in the same manner as for other antiplatelet agents.

Use in Patients with History of Stroke, TIA, or ICH
In the TRA 2°P study, patients with a history of ischemic stroke had a higher rate for ICH on ZONTIVITY than on placebo. ZONTIVITY is contraindicated in patients with a history of stroke, TIA, or ICH [see Contraindications (4)].

Other Adverse Reactions
Adverse reactions other than bleeding were evaluated in 19,632 patients treated with ZONTIVITY [13,186 patients in the TRA 2°P study and 6,446 patients in the TRA•CER (Thrombin Receptor Antagonist for Clinical Event Reduction in Acute Coronary Syndrome) study]. Adverse events other than bleeding that occurred at a rate that was at least 2% in the ZONTIVITY group and also 10% greater than the rate in the placebo group are shown in Table 2.

Table 2: TRA 2°P / TRA•CER - Percentage of Patients Reporting Non-hemorrhagic Adverse Reactions at a Rate at Least 2% in the ZONTIVITY Group and at Least 10% Greater than Placebo
 | ZONTIVITY N=19,632 | Placebo N=19,607
 | n (%) | n (%)
Anemia | 982 (5.0) | 783 (4.0)
Depression | 477 (2.4) | 405 (2.1)
Rashes, Eruptions, and Exanthemas | 439 (2.2) | 395 (2.0)

The following adverse reactions occurred at a rate less than 2% in the ZONTIVITY group but at least 40% greater than placebo. In descending order of rate in the ZONTIVITY group: iron deficiency, retinopathy or retinal disorder, and diplopia/oculomotor disturbances.

An increased rate of diplopia and related oculomotor disturbances was observed with ZONTIVITY treatment (30 subjects, 0.2%) vs. placebo (10 subjects, 0.06%). While some cases resolved during continued treatment, information on resolution of symptoms was not available for some cases.

7 DRUG INTERACTIONS

7.1 Effects of Other Drugs on ZONTIVITY

Vorapaxar is eliminated primarily by metabolism, with contributions from CYP3A4 and CYP2J2.

Strong CYP3A Inhibitors
Avoid concomitant use of ZONTIVITY with strong inhibitors of CYP3A (e.g., ketoconazole, itraconazole, posaconazole, clarithromycin, nefazodone, ritonavir, saquinavir, nelfinavir, indinavir, boceprevir, telaprevir, telithromycin and conivaptan) [see Warnings and Precautions (5.2) and Clinical Pharmacology (12.3)] .

Strong CYP3A Inducers
Avoid concomitant use of ZONTIVITY with strong inducers of CYP3A (e.g., rifampin, carbamazepine, St. John's Wort and phenytoin) [see Warnings and Precautions (5.2) and Clinical Pharmacology (12.3)].

8 USE IN SPECIFIC POPULATIONS

8.1 Pregnancy

TERATOGENIC EFFECTS

Risk Summary
Based on the potential for serious adverse reactions (such as maternal bleeding/hemorrhage) and the long half-life which makes it effectively irreversible, discontinue vorapaxar when pregnancy is detected and initiate alternative therapy with a shorter duration of action [see Warnings and Precautions (5.1) and Clinical Pharmacology (12.1, 12.2)] . Available data from postmarketing experience with ZONTIVITY use in pregnant women are insufficient to evaluate for a drug-associated risk of major birth defects, miscarriage, or adverse maternal or fetal outcomes. In animal reproduction studies, no embryo/fetal toxicities, malformations or maternal toxicities were observed in rats and rabbits exposed during the period of organogenesis at exposures 56 times and 26 times, respectively, the human systemic exposure at the recommended human dose (RHD) (see Data).

The estimated background risk of major birth defects and miscarriage for the indicated population is unknown. All pregnancies have a background risk of birth defect, loss, or other adverse outcomes. In the U.S. general population, the estimated background risk of major birth defects and miscarriage in clinically recognized pregnancies is 2% to 4% and 15% to 20%, respectively.

Data

Animal Data
In the rat embryo/fetal developmental toxicity study, pregnant rats received daily oral doses of vorapaxar at 0, 5, 25, and 75 mg/kg from implantation to closure of the fetal hard palate (6th to 17th day of gestation). Maternal systemic exposures were approximately 0, 7, 56, and 285 times greater than exposures in women treated at the RHD based on AUC. No embryo/fetal toxicities, malformations, or maternal toxicities were observed in rats receiving exposures up to 56 times the human systemic exposure at the RHD.

In the rabbit embryo/fetal developmental toxicity study, pregnant rabbits received daily oral doses of vorapaxar at 0, 2, 10, or 20 mg/kg from implantation to closure of the fetal hard palate (7th to 19th day of gestation). The NOAEL for maternal and fetal toxicity was equal to or above the highest dose tested. However, an overall increase in the number of litters with any malformation was observed at the highest dose, where systemic exposures were 89-fold higher than the human exposure at RHD.

The effects of vorapaxar on prenatal and postnatal development were assessed in pregnant rats dosed at 0, 5, 25, or 50 mg/kg/day from implantation through the end of lactation. Rat pups had decreased survival and body weight gain from birth to postnatal day 4 and decreased body weight gain for the overall pre-weaning period at exposures 67 times the human exposure at the RHD. Both male and female pups displayed effects on sensory function (acoustic startle) and neurobehavioral (locomotor assay) development on post-natal day (PND) 20 and 21, but not later (PND 60, 61) in development, whereas decreased memory was observed in female pups on PND 27 at 31 times the human exposure at the RHD. In utero and lactational exposure did not affect fertility or reproductive behavior of offspring at exposures up to 67 times the RHD.

8.2 Lactation

Risk Summary
There are no data on the presence of vorapaxar or its metabolites in human milk, the effects on the breastfed infant, or the effects on milk production. When vorapaxar was administered to lactating rats, vorapaxar was actively secreted in the milk of rats. When a drug is present in animal milk, it is likely the drug will be present in human milk. Because of the potential for serious adverse reactions in the breastfed infant, such as bleeding, advise patients that breastfeeding is not recommended during treatment with ZONTIVITY.

8.4 Pediatric Use

The safety and effectiveness of ZONTIVITY in pediatric patients have not been established.

8.5 Geriatric Use

In TRA 2°P, in post-MI or PAD patients without a history of stroke or TIA, 33% of patients were ≥65 years of age and 9% were ≥75 years of age. The relative risk of bleeding (ZONTIVITY compared with placebo) was similar across age groups. No overall differences in safety or effectiveness were observed between these patients and younger patients. ZONTIVITY increases the risk of bleeding in proportion to a patient's underlying risk. Because older patients are generally at a higher risk of bleeding, consider patient age before initiating ZONTIVITY [see Adverse Reactions (6.1)].

8.6 Renal Impairment

No dose adjustment is required in patients with renal impairment [see Clinical Pharmacology (12.3)].

8.7 Hepatic Impairment

No dose adjustment is required in patients with mild and moderate hepatic impairment. Based on the increased inherent risk of bleeding in patients with severe hepatic impairment, ZONTIVITY is not recommended in such patients [see Warnings and Precautions (5.1) and Clinical Pharmacology (12.3)].

10 OVERDOSAGE

There is no known treatment to reverse the antiplatelet effect of ZONTIVITY, and neither dialysis nor platelet transfusion can be expected to be beneficial if bleeding occurs after overdose. Inhibition of platelet aggregation can be expected for weeks after discontinuation of normal dosing [see Clinical Pharmacology (12.2)] . There is no standard test available to assess the risk of bleeding in an overdose situation.

11 DESCRIPTION

ZONTIVITY contains vorapaxar sulfate, a tricyclic himbacine-derived selective inhibitor of platelet aggregation mediated by PAR-1.

The chemical name of vorapaxar sulfate is ethyl [(1R,3aR,4aR,6R,8aR,9S,9aS)-9-{(1E)-2-[5-(3-fluorophenyl)pyridin-2-yl]ethen-1-yl}-1-methyl-3-oxododecahydronaphtho[2,3-c]furan-6-yl]carbamate sulfate. The empirical formula is C29H33FN2O4∙H2SO4, and its molecular weight is 590.7. The structural formula is:

Vorapaxar sulfate is a white to off-white solid. Vorapaxar sulfate is freely soluble in methanol and slightly soluble in ethanol, acetone, 2-propanol, and acetonitrile. In aqueous solution, it is slightly soluble in pH 1; its solubility decreases with increasing pH. ZONTIVITY tablets are formulated with vorapaxar sulfate, but during manufacture and storage, partial conversion from vorapaxar sulfate to vorapaxar free base may occur.

ZONTIVITY is available for oral use as tablets containing 2.08 mg of vorapaxar, which is equivalent to 2.5 mg of vorapaxar sulfate.

Each film-coated tablet of ZONTIVITY contains the following inactive ingredients: lactose monohydrate, microcrystalline cellulose, croscarmellose sodium, povidone, and magnesium stearate. In addition, the film coating contains the following inactive ingredients: lactose monohydrate, hypromellose, titanium dioxide, triacetin (glycerol triacetate), and iron oxide yellow.

12 CLINICAL PHARMACOLOGY

12.1 Mechanism of Action

Vorapaxar is a reversible antagonist of the protease-activated receptor-1 (PAR-1) expressed on platelets, but its long half-life makes it effectively irreversible. Vorapaxar inhibits thrombin-induced and thrombin receptor agonist peptide (TRAP)-induced platelet aggregation in in vitro studies. Vorapaxar does not inhibit platelet aggregation induced by adenosine diphosphate (ADP), collagen or a thromboxane mimetic and does not affect coagulation parameters ex vivo. PAR-1 receptors are also expressed in a wide variety of cell types, including endothelial cells, neurons, and smooth muscle cells, but the pharmacodynamic effects of vorapaxar in these cell types have not been assessed.

12.2 Pharmacodynamics

At the recommended dose, ZONTIVITY achieves ≥80% inhibition of TRAP-induced platelet aggregation within one week of initiation of treatment. The duration of platelet inhibition is dose- and concentration-dependent. Inhibition of TRAP-induced platelet aggregation at a level of 50% can be expected at 4 weeks after discontinuation of daily doses of ZONTIVITY 2.08 mg, consistent with the terminal elimination half-life of vorapaxar [see Clinical Pharmacology (12.3)] .

In healthy volunteer studies, no changes in platelet P-selectin and soluble CD40 ligand (sCD40L) expression or coagulation test parameters (TT, PT, aPTT, ACT, ECT) occurred after single- or multiple- dose (28 days) administration of vorapaxar. No meaningful changes in P-selectin, sCD40L, or hs-CRP concentrations were observed in patients treated with vorapaxar in the phase 2/3 clinical trials.

Evaluation of Vorapaxar on QTc Interval

The effect of vorapaxar on the QTc interval was evaluated in a thorough QT study and in other studies. Vorapaxar had no effect on the QTc interval at single doses up to 48 times the recommended dose.

12.3 Pharmacokinetics

Vorapaxar exposure increases in an approximately dose-proportional manner following single doses up to 16 times the recommended dose. Vorapaxar pharmacokinetics are similar in healthy subjects and patients.

Absorption
After oral administration of a single ZONTIVITY 2.08 mg dose under fasted conditions, peak concentrations (Cmax) occur at 1 hour post-dose (range: 1 to 2 h). The mean absolute bioavailability as determined from a microdosing study is approximately 100%.

Ingestion of vorapaxar with a high-fat meal resulted in no meaningful change in AUC with a small (21%) decrease in Cmax and delayed time to peak concentration (45 minutes). ZONTIVITY may be taken with or without food.

Distribution
The mean volume of distribution of vorapaxar is approximately 424 liters (95% CI: 351-512). Vorapaxar and the major circulating active metabolite, M20, are extensively bound (≥99%) to human plasma proteins. Vorapaxar is highly bound to human serum albumin and does not preferentially distribute into red blood cells.

Metabolism
Vorapaxar is eliminated by metabolism via CYP3A4 and CYP2J2. The major active circulating metabolite is M20 (monohydroxy metabolite) and the predominant metabolite identified in excreta is M19 (amine metabolite). The systemic exposure of M20 is ~20% of the exposure to vorapaxar.

Excretion
The primary route of elimination is through the feces. In a 6-week study, 84% of the administered radiolabeled dose was recovered as total radioactivity with 58% collected in feces and 25% in urine. Vorapaxar is eliminated primarily in the form of metabolites, with no unchanged vorapaxar detected in urine.

Vorapaxar exhibits multi-exponential disposition with an effective half-life of 3-4 days and an apparent terminal elimination half-life of 8 days. Steady-state is achieved by 21 days following once-daily dosing with an accumulation of 5- to 6-fold. The apparent terminal elimination half-life for vorapaxar is approximately 8 days (range 5-13 days) and is similar for the active metabolite. The terminal elimination half-life is important to determine the time to offset the pharmacodynamic effect [see Clinical Pharmacology (12.2)] .

Specific Populations
The effects of intrinsic factors on the pharmacokinetics of vorapaxar are presented in Figure 2 [see Use in Specific Populations (8.5, 8.6, 8.7)] .

In general, effects on the exposure of vorapaxar based on age, race, gender, weight, and moderate renal insufficiency were modest (20-40%; see Figure 2). No dose adjustments are necessary based upon these factors. Because of the inherent bleeding risks in patients with severe hepatic impairment, ZONTIVITY is not recommended in such patients [see Warnings and Precautions (5.1) and Use in Specific Populations (8.7)] .

Figure 2: Effect of Intrinsic Factors on the Pharmacokinetics of Vorapaxar

† See Warnings and Precautions. (5.1) and Use in Specific Populations. (8.7)

Drug Interactions [see also Drug Interactions (7)]
Anticoagulants and Antiplatelet Agents
An interaction study with vorapaxar and warfarin in healthy subjects did not demonstrate a clinically significant pharmacokinetic or pharmacodynamic interaction [see Warnings and Precautions (5.1) and Figure 4] .

Vorapaxar did not affect prasugrel pharmacokinetics and prasugrel did not affect vorapaxar pharmacokinetics following multiple-dose administration at steady-state [see Warnings and Precautions (5.1) and Figures 3 and 4] . The pharmacokinetic interaction between vorapaxar and clopidogrel has not been evaluated. However, the use of vorapaxar on a background of clopidogrel is supported by the clinical data from TRA 2°P and TRA•CER [see Adverse Reactions (6.1) and Clinical Studies (14)] .

Effects of Other Drugs on Vorapaxar
The effects of other drugs on the pharmacokinetics of vorapaxar are presented in Figure 3 as change relative to vorapaxar administered alone (test/reference). Phase 3 data suggest that coadministration of a weak or moderate CYP3A inhibitor with vorapaxar does not increase bleeding risk or alter the efficacy of vorapaxar. No dose adjustment for ZONTIVITY is required in patients taking weak to moderate inhibitors of CYP3A.

Figure 3: Effects of Other Drugs on the Pharmacokinetics of Vorapaxar

† See Warnings and Precautions. (5.2) and Drug Interactions. (7.1)

‡ See Dosage and Administration. (2.2)

Effects of Vorapaxar on Other Drugs
In vitro metabolism studies demonstrate that vorapaxar or M20 is unlikely to cause clinically significant inhibition or induction of major CYP isoforms or inhibition of OATP1B1, OATP1B3, BCRP, OAT1, OAT3, and OCT2 transporters.

Specific in vivo effects on the pharmacokinetics of digoxin, warfarin, rosiglitazone and prasugrel are presented in Figure 4 as a change relative to the interacting drug administered alone (test/reference). Vorapaxar is a weak inhibitor of the intestinal P-glycoprotein (P-gp) transporter. No dosage adjustment of digoxin or ZONTIVITY is required.

Figure 4: Effects of Vorapaxar on the Pharmacokinetics of Other Drugs

† See Warnings and Precautions. (5.1)

‡ See Dosage and Administration. (2.2)

13 NONCLINICAL TOXICOLOGY

13.1 Carcinogenesis, Mutagenesis, Impairment of Fertility

Carcinogenesis
Carcinogenicity studies were conducted in rats and mice dosed orally with vorapaxar for two years. Male and female rats dosed at 0, 3, 10 or 30 mg/kg/day showed no carcinogenic potential at systemic exposures (AUC) in males and females that were 9- and 29-fold, respectively, the human systemic exposure at the RHD. In male and female mice dosed at 0, 1, 5, and 15 mg/kg/day, vorapaxar showed no carcinogenic potential at systemic exposures (AUC) that were up to 30-fold the human systemic exposure.

Mutagenesis
Vorapaxar was not mutagenic in the Ames bacterial reverse mutation assay and not clastogenic in an in vitro human peripheral blood lymphocyte assay or an in vivo mouse micronucleus assay after intraperitoneal administration.

Impairment of Fertility
Fertility studies in rats showed that vorapaxar had no effect on either male or female fertility at doses up to 50 mg/kg/day, a dose resulting in systemic exposures (AUC) in male and female rats that are 40 and 67 times, respectively, the human systemic exposure at the RHD.

13.2 Animal Pharmacology

Vorapaxar did not increase bleeding time in non-human primates when administered alone. Bleeding time was prolonged slightly with administration of aspirin or aspirin plus vorapaxar. The combination of aspirin, vorapaxar, and clopidogrel produced significant prolongation of bleeding time. Transfusion of human platelet rich plasma normalized bleeding times with partial recovery of ex vivo platelet aggregation induced with arachidonic acid, but not induced with ADP or TRAP. Platelet poor plasma had no effect on bleeding times or platelet aggregation [see Warnings and Precautions (5.1)].

14 CLINICAL STUDIES

The clinical evidence for the effectiveness of ZONTIVITY is supported by TRA 2°P - TIMI 50. TRA 2°P was a multicenter, randomized, double-blind, placebo-controlled study conducted in patients who had evidence or a history of atherosclerosis involving the coronary (spontaneous MI ≥2 weeks but ≤12 months prior), cerebral (ischemic stroke), or peripheral vascular (documented peripheral arterial disease [PAD]) systems. Patients were randomized to receive daily treatment with ZONTIVITY (n=13,225) or placebo (n=13,224) in addition to standard of care. The study's primary endpoint was the composite of cardiovascular death, MI, stroke, and urgent coronary revascularization (UCR). The composite of cardiovascular death, MI, and stroke was assessed as key secondary endpoint. The median follow-up was 2.5 years (up to 4 years).

The findings in all randomized patients for the primary efficacy composite endpoint show a 3-year K-M event rate of 11.2% in the ZONTIVITY group compared to 12.4% in the placebo group (hazard ratio [HR]: 0.88; 95% confidence interval [CI], 0.82 to 0.95; p=0.001).

The findings for the key secondary efficacy endpoint show a 3-year Kaplan-Meier (K-M) event rate of 9.3% in the ZONTIVITY group compared to 10.5% in placebo group (HR 0.87; 95% CI, 0.80 to 0.94; p<0.001).

Although TRA 2°P was not designed to evaluate the relative benefits and risks of ZONTIVITY in individual patient subgroups, patients with a history of stroke or TIA showed an increased risk of ICH. Of the patients who comprised the post-MI and PAD strata and had no baseline history of stroke or TIA,10,080 were randomized to treatment with ZONTIVITY and 10,090 to placebo. These patients were 89% Caucasian, 22% female, and 33% ≥65 years of age, with a median age of 60 years. The population included patients with diabetes (24%) and patients with hypertension (65%). Of the patients who qualified for the trial with MI without a history of stroke or TIA, 98% were receiving aspirin, 78% were receiving a thienopyridine, and 77% were receiving both aspirin and a thienopyridine when they enrolled in the trial. Of the patients who qualified for the trial with PAD without a history of stroke or TIA, 88% were receiving aspirin, 35% were receiving a thienopyridine, and 27% were receiving both aspirin and a thienopyridine when they enrolled.

In post-MI or PAD patients without a history of stroke or TIA the 3-year K-M event rate for the primary efficacy endpoint (composite of time to first CV death, MI, stroke, or UCR) was 10.1% in the ZONTIVITY group compared to 11.8% in the placebo group (HR 0.83; 95% CI, 0.76 to 0.90; p<0.001) (see Figure 5 and Table 3).

The results for the key secondary efficacy endpoint (composite of time to first CV death, MI, or stroke) show a 3-year K-M event rate of 7.9% in the ZONTIVITY group compared to 9.5% in the placebo group (HR 0.80; 95% CI, 0.73 to 0.89; p<0.001) (see Table 3).

The effect of chronic dosing with ZONTIVITY on the primary and key secondary endpoints was maintained for the duration of the trial (median follow up 2.5 years, up to 4 years).

Figure 5: Time to First Occurrence of the Composite Endpoint of CV Death, MI, Stroke or UCR in Post-MI or PAD Patients without a History of Stroke or TIA in TRA 2°P

Table 3: TRA 2°P: Time to First Event in Post-MI or PAD Patients without a History of Stroke or TIA
 | Placebo (n=10,090) |  | ZONTIVITY (n=10,080)
Endpoints | Patients with events [Each patient was counted only once (first component event) in the component summary that contributed to the primary efficacy endpoint.] (%) | K-M % [K-M estimate at 1,080 days.] | Patients with events (%) | K-M % | Hazard Ratio [Hazard ratio is ZONTIVITY group versus placebo group.] , [Cox proportional hazard model with covariates treatment and stratification factors (qualifying atherosclerotic disease and planned thienopyridine use).] (95% CI) | p-value
Primary Composite Efficacy Endpoint (CV death/MI/stroke/UCR) , | 1073 (10.6%) | 11.8% | 896 (8.9%) | 10.1% | 0.83 (0.76-0.90) | <0.001
Secondary Composite Efficacy Endpoint (CV death/MI/stroke) , | 851 (8.4%) | 9.5% | 688 (6.8%) | 7.9% | 0.80 (0.73-0.89) | <0.001
Other Secondary Efficacy Endpoints (first occurrences of specified event at any time) [Including patients who could have had other non-fatal events or subsequently died.]
CV Death | 239 (2.4%) | 2.8% | 205 (2.0%) | 2.4% | 0.86 (0.71-1.03)
MI | 569 (5.6%) | 6.4% | 470 (4.7%) | 5.4% | 0.82 (0.73-0.93)
Stroke | 145 (1.4%) | 1.6% | 98 (1.0%) | 1.2% | 0.67 (0.52-0.87)
UCR | 283 (2.8%) | 3.0% | 249 (2.5%) | 2.8% | 0.88 (0.74-1.04)

In post-MI or PAD patients who survived an on-study efficacy event, the incidence of subsequent events was lower with ZONTIVITY.

The time from the prior MI to randomization had no relationship to the treatment benefit for the primary study outcome.

A range of demographic, concurrent baseline medications, and other treatment differences were examined for their influence on outcomes as shown in Figure 6. Such analyses must be interpreted cautiously, as differences can reflect the play of chance among a large number of analyses.

Figure 6: Subgroup Analyses (Primary Endpoints) of the TRA 2°P Post-MI or PAD Patients without a History of Stroke or TIA

16 HOW SUPPLIED/STORAGE AND HANDLING

ZONTIVITY tablets, 2.08 mg vorapaxar, are yellow, oval-shaped, film-coated tablets with "351" on one side.

They are supplied as follows:

- NDC 66992-208-30 bottles of 30 tablets
- NDC 66992-208-90 bottles of 90 tablets

Storage of bottles
Store at 20-25°C (68-77°F), excursions permitted between 15-30°C (between 59-86°F). [See USP Controlled Room Temperature.] Store tablets in the original package with the bottle tightly closed. Keep the desiccant in the bottle to protect from moisture.

Storage of blisters
Store at 20-25°C (68-77°F), excursions permitted between 15-30°C (between 59-86°F). [See USP Controlled Room Temperature.] Store in the original package until use.

17 PATIENT COUNSELING INFORMATION

Advise the patient to read the FDA-approved Patient Labeling (Medication Guide).

Benefits and Risks

- Summarize the benefits and potential side effects of ZONTIVITY.
- Tell patients to take ZONTIVITY exactly as prescribed.
- Inform patients not to discontinue ZONTIVITY without discussing it with the prescribing physician.
- Tell patients to read the Medication Guide.

Bleeding
Inform patients that they:

- May bleed and bruise more easily.
- Should report any unanticipated, prolonged or excessive bleeding, or blood in their stool or urine.

Invasive Procedures
Instruct patients to:

- Inform physicians and dentists that they are taking ZONTIVITY before any surgery or dental procedure.
- Tell the doctor performing any surgery or dental procedure to talk to the prescribing physician before stopping ZONTIVITY.

Concomitant Medications
Tell patients to list all prescription medications, over-the-counter medications, or dietary supplements they are taking or plan to take so that the physician knows about other treatments that may affect bleeding risk.

Lactation
Advise patients that breastfeeding is not recommended during treatment with Zontivity

Manufactured for:
WraSer Pharmaceuticals
Ridgeland, MS 39157
www.wraser.com

Medication Guide
ZONTIVITY® (zon-TIV-iti)
(vorapaxar)
Tablets

Read this Medication Guide before you start taking ZONTIVITY and each time you get a refill. There may be new information. This information does not take the place of talking with your doctor about your medical condition or your treatment.

What is the most important information I should know about ZONTIVITY?

ZONTIVITY is used to lower your chance of having another serious problem with your heart or blood vessels, but ZONTIVITY (and similar drugs) can cause bleeding that can be serious and lead to death.

Call your doctor right away if you have any of these signs or symptoms of bleeding while taking ZONTIVITY:

- bleeding that is severe or that you cannot control
- pink, red, or brown urine
- vomiting blood or your vomit looks like "coffee grounds"
- red or black stools (looks like tar)
- coughing up blood or blood clots.

While you take ZONTIVITY and for about 4 weeks after your treatment with ZONTIVITY is stopped:

- you may bruise and bleed more easily (nose bleeds may be common)
- it will take longer than usual for any bleeding to stop.

Do not take ZONTIVITY if you:

- have had a stroke or "mini stroke" (also known as transient ischemic attack or TIA)
- have had bleeding in your brain
- currently have unusual bleeding, such as bleeding in your head, stomach or intestines (an ulcer).

If you have a stroke, TIA, or bleeding in your brain while taking ZONTIVITY your doctor should stop your treatment with ZONTIVITY. Follow your doctor's instructions about stopping ZONTIVITY.

Do not stop taking ZONTIVITY without talking to the doctor who prescribed it for you.

What is ZONTIVITY?

ZONTIVITY is a prescription medicine used to treat people who have

- had a heart attack or
- reduced blood flow in their legs (peripheral arterial disease).

ZONTIVITY is used with aspirin and/or clopidogrel to lower your chance of having another serious problem with your heart or blood vessels, such as heart attack, stroke, or death.

It is not known if ZONTIVITY is safe and effective in children.

What should I tell my doctor before taking ZONTIVITY?

Before you take ZONTIVITY, tell your doctor if you:

- have had bleeding problems or history of stomach ulcers
- have had a stroke or "mini-stroke" (also known as transient ischemic attack or TIA)
- have had any recent serious injury or surgery
- plan to have surgery or a dental procedure
- have kidney problems or severe liver problems
- are pregnant or plan to become pregnant. It is not known if ZONTIVITY will harm your unborn baby.
- are breastfeeding or plan to breastfeed. It is not known if ZONTIVITY passes into your breast milk. You and your doctor should decide if you will take ZONTIVITY or breastfeed. You should not do both.

Tell all of your doctors and dentists that you are taking ZONTIVITY. They should talk to the doctor who prescribed ZONTIVITY for you before you have any surgery or dental procedure.

Tell your doctor about all the medicines you take, including prescription and over-the-counter medicines, vitamins, dietary or herbal supplements. Taking ZONTIVITY with certain other medicines may increase your risk of bleeding and may affect how ZONTIVITY works.

Know the medicines you take. Keep a list of them to show your doctor and pharmacist when you get a new medicine.

How should I take ZONTIVITY?

Take ZONTIVITY exactly as prescribed by your doctor.

- Take ZONTIVITY 1 time each day.
- Take ZONTIVITY with or without food.
- Take ZONTIVITY with aspirin and/or clopidogrel as prescribed by your doctor.
- Do not stop taking ZONTIVITY without first talking to the doctor who prescribed it for you.
- If you take too much ZONTIVITY, call your doctor, or go to the nearest emergency room right away.

What are the possible side effects of ZONTIVITY?

- See " What is the most important information I should know about ZONTIVITY?"
- Anemia (low level of red blood cells)
- Depression
- Rash

These are not all the possible side effects of ZONTIVITY.

Call your doctor for medical advice about side effects. You may report side effects to FDA at 1-800-FDA-1088.

How should I store ZONTIVITY?

- Store ZONTIVITY at room temperature between 68°F to 77°F (20°C to 25°C).
- Keep ZONTIVITY in the bottle it comes in.
- Keep the bottle tightly closed.
- The ZONTIVITY bottle contains a desiccant packet to help keep your medicine dry (protect it from moisture). Keep the desiccant packet in the bottle. Do not throw away the desiccant packet.
- Store blister packs of ZONTIVITY in the original package it comes in.

Keep ZONTIVITY and all medicines out of the reach of children.

You can ask your doctor or pharmacist for information about ZONTIVITY that is written for health professionals.

For more information, go to www.zontivity.com or call 1-800-988-6115.

What are the ingredients in ZONTIVITY?
Active ingredient: vorapaxar sulfate

Inactive ingredients:
Tablet: lactose monohydrate, microcrystalline cellulose, croscarmellose sodium, povidone, and magnesium stearate

Film coating: lactose monohydrate, hypromellose, titanium dioxide, triacetin (glycerol triacetate), and iron oxide yellow

This Medication Guide has been approved by the U.S. Food and Drug Administration.

Manufactured for:
WraSer Pharmaceuticals
Ridgeland MS 39157
www.wraser.com

Revised: 10/2022

PRINCIPAL DISPLAY PANEL - 30 Tablet Bottle Label

NDC 66992-208-30

Zontivity®
(vorapaxar) tablets

2.08 mg*

Dispense the accompanying
Medication Guide to each patient.

*Each tablet contains 2.08 mg
vorapaxar, equivalent to 2.5 mg
vorapaxar sulfate.

Rx only

30 Tablets

WraSer Pharmaceuticals